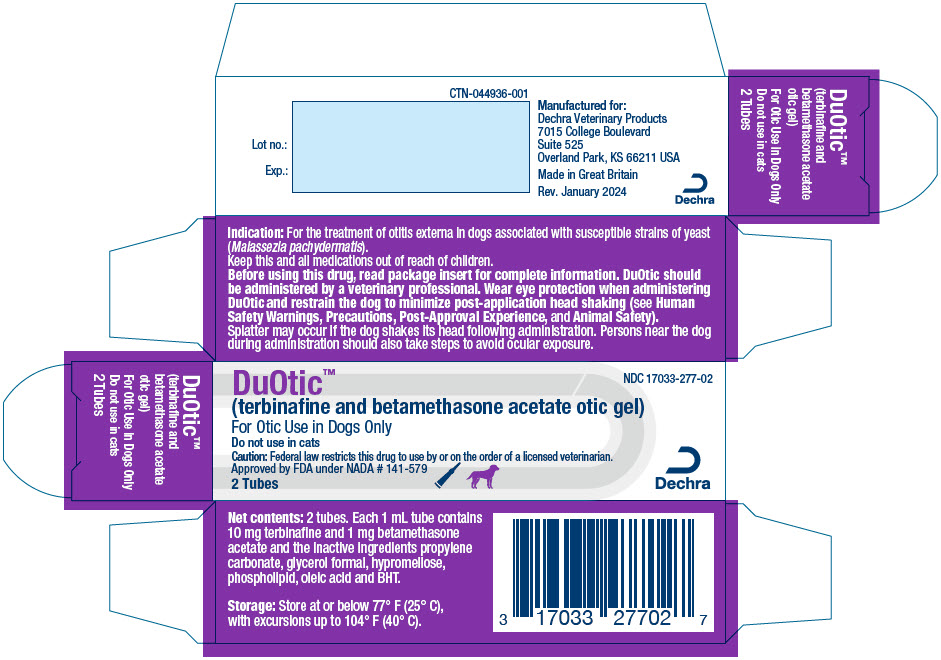 DRUG LABEL: DuOtic
NDC: 17033-277 | Form: GEL
Manufacturer: Dechra Veterinary Products
Category: animal | Type: PRESCRIPTION ANIMAL DRUG LABEL
Date: 20250122

ACTIVE INGREDIENTS: Terbinafine 10 mg/1 mL; Betamethasone Acetate 1 mg/1 mL

DuOtic™
(terbinafine and betamethasone acetate otic gel)

Antifungal, anti-inflammatory

For Otic Use in Dogs Only
Do not use in cats

CAUTION:

Federal law restricts this drug to use by or on the order of a licensed veterinarian.

DESCRIPTION:

DuOtic™ contains 10 mg terbinafine and 1 mg betamethasone acetate per mL and the inactive ingredients propylene carbonate, glycerol formal, hypromellose, phospholipid, oleic acid and butylated hydroxytoluene in an off-white to slightly yellow translucent gel.

INDICATION:

DuOtic™ is indicated for the treatment of otitis externa in dogs, associated with susceptible strains of yeast (Malassezia pachydermatis).

DOSAGE AND ADMINISTRATION:

DuOtic™ should be administered by a veterinary professional. Wear eye protection when administering DuOtic™ (see Human Safety Warnings, Precautions, Post-approval Experience, and Target Animal Safety).

Splatter may occur if the dog shakes its head following administration. Persons near the dog during administration should also take steps to avoid ocular exposure.

1. Clean and dry the external ear canal before administering the initial dose of the product.
2. Verify the tympanic membrane is intact prior to each administration (see Precautions, Contraindications, Target Animal Safety and Post-approval Experience).
3. Administer one dose (1 tube) per affected ear. Repeat administration in 7 days.
4. Open tube by twisting the soft tip. Insert the flexible tip in the affected external ear canal and squeeze entire tube contents into the external ear canal. After application, gently massage the base of the ear to allow the gel to penetrate the lower part of the ear canal.
5. Restrain dog to minimize post-application head shaking to reduce potential for splatter of product, and accidental eye exposure in people and dogs (see Post-Approval Experience and Target Animal Safety).
6. Do not clean the ear canal for 45 days after the initial administration to allow contact of the gel with the ear canal. Cleaning the ear may affect product effectiveness (see Effectiveness). If alternative otic therapies are required, it is recommended to clean the ear(s) before application of those therapies.

CONTRAINDICATIONS:

Do not use in dogs with known tympanic perforation (see Precautions). Do not use in dogs with a hypersensitivity to terbinafine or corticosteroids.

WARNINGS:

Human Safety Warnings:

DuOtic™ may cause eye injury and irritation (see Precautions, Post-approval Experience and Target Animal Safety).

In case of accidental eye contact, flush thoroughly with water for at least 15 minutes. If wearing contact lenses, rinse eyes first then remove contact lenses and continue to rinse. If symptoms develop, seek medical advice.

Not for use in humans. Keep this and all medications out of reach of children. Consult a physician in case of accidental ingestion by humans. In case of accidental skin contact, wash area thoroughly with water.

PRECAUTIONS:

Wear eye protection when administering DuOtic™ and restrain the dog to minimize post-application head shaking. Reducing the potential for splatter of product will help prevent accidental eye exposure in people and dogs and help to prevent eye injury (see Human Safety Warnings, Post-approval Experience and Target Animal Safety). Avoid hand-to-eye contact.

Proper patient selection is important when considering the benefits and risks of using DuOtic™. The use of DuOtic™ in dogs with perforated tympanic membranes has not been evaluated. The integrity of the tympanic membrane should be confirmed before administering each dose of this product. Reevaluate the dog if hearing loss or signs of vestibular dysfunction are observed during treatment.

Changes to the middle ear, such as ulceration of the mucosal lining, have been associated with administration of Osurnia® (florfenicol, terbinafine, betamethasone acetate). The presentation and concentrations of terbinafine and betamethasone acetate in DuOtic™ are identical to the concentrations of these active ingredients in Osurnia® (see Target Animal Safety).

Signs of tympanic membrane rupture, internal ear disease such as head tilt, ataxia, nystagmus, facial paralysis, and keratoconjunctivitis sicca have also been reported in relation to the administration of Osurnia® (see Post-approval Experience).

Do not administer orally.

Use of topical otic corticosteroids has been associated with adrenocortical suppression and iatrogenic hyperadrenocorticism in dogs (see Target Animal Safety).

Use with caution in dogs with impaired hepatic function (see Target Animal Safety and Adverse Reactions).

The safe use of DuOtic™ has not been evaluated in dogs that are pregnant, lactating or intended for breeding.

ADVERSE REACTIONS:

The following adverse reactions were reported during the course of a US field study for treatment of otitis externa in dogs treated with DuOtic™ with 1 tube per affected ear(s) and repeated after 7 days:

Number (%) of dogs with Adverse Reactions by Treatment
Adverse Reaction | DuOtic™ (n=120) | Control (n=119)
Elevated alanine aminotransferase [Four dogs were reported to have an increase in alanine aminotransferase at Study Exit. The levels reported in subsequent clinical chemistries returned to normal in three dogs, while no follow up was performed for the fourth dog.] | 4 (3.3%) | 0 (0.0%)
Conjunctivitis | 1 (0.8%) | 0 (0.0%)
Ocular discharge | 1 (0.8%) | 2 (1.7%)
Ear discharge | 0 (0.0%) | 1 (0.8%)
Ear pruritus | 3 (2.5%) | 4 (3.4%)

Post-Approval Experience:

The following adverse events are based on post-approval adverse drug experience reporting for Osurnia® (florfenicol, terbinafine, betamethasone acetate). The presentation and concentrations of terbinafine and betamethasone acetate in DuOtic™ are identical to the concentrations of these active ingredients in Osurnia®. Not all adverse events are reported to FDA/CVM. It is not always possible to reliably estimate the adverse event frequency or establish a causal relationship to product exposure using this data.

In humans, accidental exposure leading to corneal ulcers and other ocular injuries such as eye irritation, burning, stinging, and itchiness have been reported to occur when the dog shook its head after application of Osurnia®.

In dogs, the adverse events reported for Osurnia® are presented below in decreasing order of reporting frequency:

Deafness, ear discharge, pinnal irritation and ear pain, emesis, head shaking, internal ear disorder (head tilt and vestibular), ataxia, vocalization, corneal ulcer, keratoconjunctivitis sicca, nystagmus, tympanic rupture, and cranial nerve disorder (facial paralysis).

Osurnia® is not approved for use in cats. The adverse events reported following extra-label use in cats are presented below in decreasing order of reporting frequency:

Ataxia, anorexia, Horner's syndrome (third eyelid prolapse and miosis), internal ear disorder (head tilt and vestibular), anisocoria, lethargy, head shake, emesis, nystagmus, deafness, and tympanic rupture.

CONTACT INFORMATION:

To report suspected adverse drug events and/or to obtain a copy of the Safety Data Sheet (SDS) or for technical assistance, contact Dechra at 1-866-933-2472.

For additional information about adverse drug experience reporting for animal drugs, contact FDA at 1-888-FDA-VETS or online at www.fda.gov/reportanimalae.

INFORMATION FOR DOG OWNERS:

Owners should be aware that adverse reactions may occur following administration of DuOtic™ and should observe their dog for signs such as deafness, ear pain and irritation, vomiting, head shaking, head tilt, incoordination, eye pain and ocular discharge (see Animal Safety and Post-approval Experience). Owners should be advised to contact their veterinarian if any of the above signs are observed.

Owners should also be informed that splatter may occur if the dog shakes its head following administration of DuOtic™ which may lead to eye exposure. As a result, eye injuries in humans and dogs have been reported including corneal ulcers following the use of a similar product (Osurnia®). Owners should be careful to avoid ocular exposure (see Precautions and Post-approval Experience).

CLINICAL PHARMACOLOGY:

DuOtic™ is a fixed combination of two active ingredients: terbinafine (antifungal) and betamethasone acetate (steroidal anti-inflammatory). Terbinafine is an antifungal which selectively inhibits the early synthesis of ergosterol. Betamethasone acetate is a glucocorticosteroid with anti-inflammatory activity.

DuOtic™ dissolves in ear wax and is slowly eliminated from the ear mechanically. Ear inflammation can increase the percutaneous absorption of active substances in DuOtic™.

In a laboratory study conducted in healthy dogs administered Osurnia® (see Target Animal Safety), low plasma concentrations of florfenicol, terbinafine, and betamethasone acetate were measurable during the first 2-4 days after administration of 1X dose, and during the first 2-7 days after administration of 5X dose. No quantifiable plasma concentrations of any of the three active ingredients were observed in the pre-dose samples of most dogs prior to second and third administrations. Although total and peak exposure in the blood tended to be highly variable between dogs, systemic drug concentrations tended to increase in a less than dose-proportional manner as the administered dose increased from 1X to 5X. The systemic exposure of terbinafine and betamethasone are not expected to be affected by the removal of florfenicol from the formulation.

MYCOLOGY:

The compatibility of the components of DuOtic™ was demonstrated in a non-interference study. An in vitro study of organisms collected from clinical cases of otitis externa in dogs determined that terbinafine inhibits the growth of Malassezia pachydermatis, a yeast commonly associated with otitis externa in dogs. The presence of betamethasone acetate in the formulation did not impair the antifungal effect of terbinafine to any clinically significant extent. In a field study (see Effectiveness), the minimum of 10 isolates from successfully treated cases with DuOtic™ was met for Malassezia pachydermatis.

EFFECTIVENESS:

Effectiveness was evaluated in 197 dogs with otitis externa associated with M. pachydermatis. The study was a placebo-controlled, randomized, double-masked, multi-center field study. One hundred and two dogs were treated with DuOtic™ and 95 dogs were treated with placebo control (saline). All dogs were evaluated for safety. Treatment (1 mL) was administered to the affected ear(s) and repeated seven days later. Prior to the first administration only, the ear(s) were cleaned with saline. Four clinical signs associated with otitis externa were evaluated: erythema, edema/swelling, erosion/ulceration, and exudate. Total clinical scores were assigned for a dog based on the severity of each clinical sign on Days 0, 7, 14, 28, and 45.

Success was determined by clinical improvement at Day 45. The success rates of the two groups were significantly different (p=0.0001); 62.31% of dogs administered DuOtic™ were successfully treated, compared to 17.84% of the dogs in the placebo group.

TARGET ANIMAL SAFETY:

The presentation and concentrations of terbinafine and betamethasone acetate in DuOtic™ are identical to the concentrations of these active ingredients in Osurnia® (florfenicol, terbinafine, betamethasone acetate), approved under NADA 141-437. Therefore, the target animal safety for DuOtic™ is supported by the target animal safety study conducted for the approval of Osurnia®.

In a target animal safety study, 24 mixed breed dogs (4 dogs/sex/group) were aurally administered 0X, 1X (1 mL/ear or 2 mL/dog with repeated administration in 7 days) or 5X (5 mL/ear or 10 mL/dog with repeated administration in 7 days) doses of Osurnia® for a total of 6 administrations in 5 weeks. All dogs remained in good health with normal hearing throughout the study. Decreased weight gain was noted in the 1X and 5X groups compared to the control group. Clinical findings included post- administration ear wetness in 1X and 5X groups and unilateral, transient brown/red discharge from one ear each in two 5X dogs, with erythema in one dog after the 4th application. Local microscopic changes in ears (without clinical effects) included: slight or moderate unilateral vesicle formation within the epithelium of the tympanic membrane in two 1X and four 5X dogs, and unilateral mucosal ulceration in the lining of the middle ear cavity in three 5X dogs. Three 5X dogs had slightly elevated ALT activity, accompanied by minimal or mild microscopic hepatocellular vacuolation (in two dogs). Cortisol response to ACTH stimulation was decreased, but within the normal reference range, in 1X dogs. The 5X dogs had a decrease in serum cortisol levels after ACTH stimulation (below normal reference range) accompanied by decreased adrenal gland and thymic weights with minimal adrenal cortical atrophy and slight (in three dogs) or moderate (in one dog also noted with slightly lower lymphocyte counts) lymphoid depletion of the thymus. The ACTH stimulation test results are consistent with systemic absorption of betamethasone resulting in a likely reversible suppression of the hypothalamic-pituitary-adrenal axis as seen with administration of exogenous corticosteroids.

STORAGE CONDITIONS:

Store at or below 77° F (25° C), with excursions up to 104° F (40° C).

HOW SUPPLIED:

DuOtic™ is a gel in a single-use tube with a flexible soft tip, supplied in cartons containing 2 or 20 tubes.

Approved by FDA under NADA # 141-579

Manufactured for:
Dechra Veterinary Products
7015 College Boulevard, Suite 525
Overland Park, KS 66211 USA

Product of Great Britain

DuOtic™ is a trademark of
Dechra Limited.

Rev. January 2024

PIL-044936-001

PRINCIPAL DISPLAY PANEL - 2 Tube Carton

NDC 17033-277-02

DuOtic™
(terbinafine and betamethasone acetate otic gel)

For Otic Use in Dogs Only

Do not use in cats

Caution: Federal law restricts this drug to use by or on the order of a licensed veterinarian.
Approved by FDA under NADA # 141-579

2 Tubes

Dechra